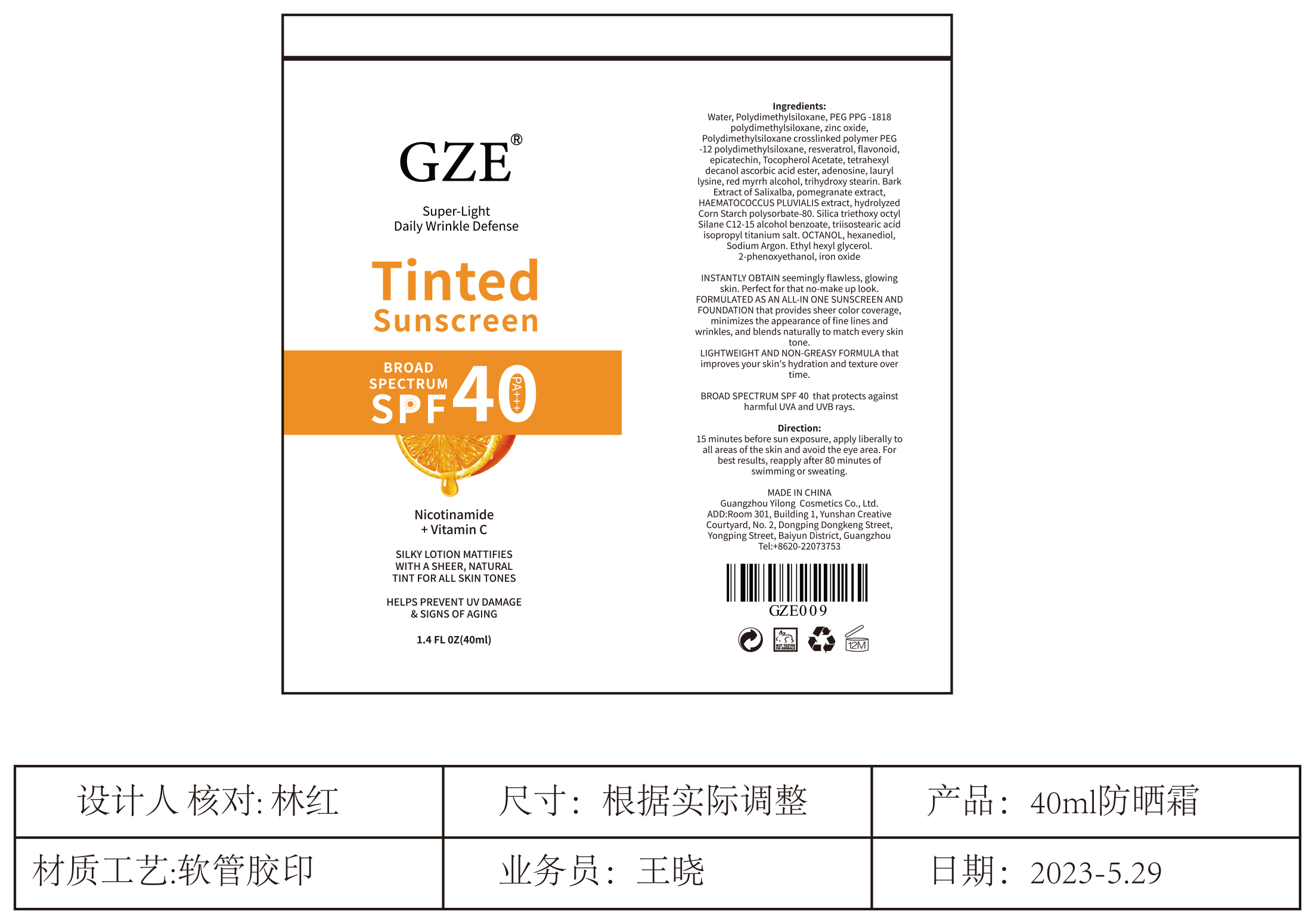 DRUG LABEL: GZE Tinted Sunscreen
NDC: 83566-101 | Form: CREAM
Manufacturer: Guangdong Aimu Biological Technology Co., Ltd
Category: otc | Type: HUMAN OTC DRUG LABEL
Date: 20231120

ACTIVE INGREDIENTS: ZINC OXIDE 3 mg/100 mL
INACTIVE INGREDIENTS: ASCORBYL TETRAISOPALMITATE; LAUROYL LYSINE; LEVOMENOL; TRIHYDROXYSTEARIN; SALIX ALBA BARK; HAEMATOCOCCUS PLUVIALIS; POLYSORBATE 80; TRIETHOXYCAPRYLYLSILANE; FERRIC OXIDE RED; PEG-12 DIMETHICONE; RESVERATROL; SOY ISOFLAVONES; EPICATECHIN; ALPHA-TOCOPHEROL ACETATE; ADENOSINE; POMEGRANATE; CAPRYLIC ALCOHOL; HEXANEDIOL; ETHYLHEXYLGLYCERIN; MALTOTETRAOSE; ALKYL (C12-15) BENZOATE; ISOPROPYL TITANIUM TRIISOSTEARATE; PHENOXYETHANOL; WATER; DIMETHICONE; EDETATE DISODIUM

GZE Tinted Sunscreen

GZE Tinted Sunscreen

ACTIVE INGREDIENT

Zinc Oxide 3%

PURPOSE

HELPS PREVENT UV DAMAGE & SIGNS OF AGING

INDICATIONS AND USAGE

SILKY LOTION MATTIFIES WITH A SHEER, NATURAL TINT FOR ALL SKIN TONES
|HELPS PREVENTUV DAMAGE& SIGNS OF AGING

WARNINGS

For external use only, if it gets into eyes accidentally, rinse with plenty of water, seek medical attention immediately if you feel unwell. Keep out of reach of children

WHEN USING

Super-Light Daily Wrinkle Defense

INSTANTLY OBTAIN seemingly flawless, glowingskin. Perfect for that no-make up look.FORMULATED AS AN ALLIN ONE SUNSCREEN ANDFOUNDATION that provides sheer color coverage,minimizes the appearance of fine lines andwrinkles, and blends naturally to match every skintone.LIGHTWEIGHT AND NON-GREASY FORMULA thatimproves your skin's hydration and texture over
time.

STOP USE

For external use only, if it gets into eyes accidentally, rinse with plenty of water, seek medical attention immediately if you feel unwell. Keep out of reach of children

Keep out of reach of children

DOSAGE AND ADMINISTRATION

Squeeze out an appropriate amount of sunscreen and spread evenly on skin.

STORAGE AND HANDLING

Store in a cool dry place

INACTIVE INGREDIENT

Water
Polydimethylsiloxane
Peg Ppg-1818polydimethylsiloxane
DIMETHICONE
PEG-12 DIMETHICONE
Resveratrol
SOY ISOFLAVONES
Epicatechin
Tocopherol Acetate
ASCORBYL TETRAISOPALMITATE
Adenosine
LAUROYL LYSINE
Red Myrrh Alcohol
TRIHYDROXYSTEARIN
Barkextract Of Salixalba
Pomegranate Extract
Haematococcus Pluvialis Extract
Hydrolyzedcorn Starch
Polysorbate-80
Silica Triethoxy Octylsilane
C12-15 Alcohol Benzoate
Triisostearic Acidisopropyl Titanium Salt
Octanol
Hexanediol
Sodium Argon
Ethyl Hexyl Glycerol
2-Phenoxyethanol
Iron Oxide